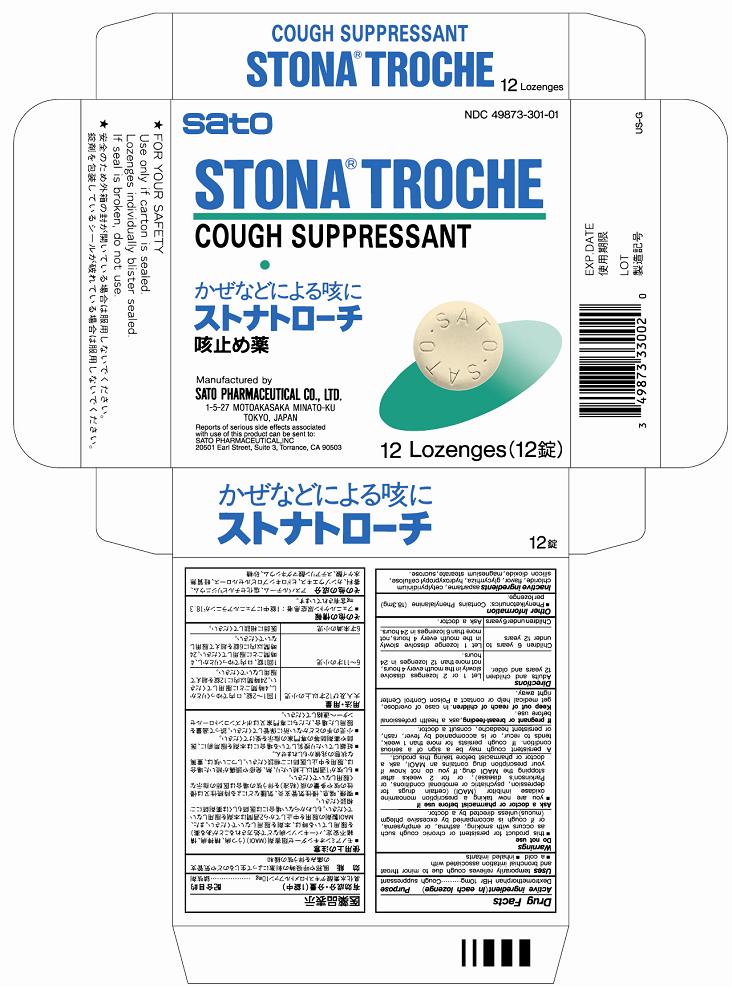 DRUG LABEL: Stona
NDC: 49873-301 | Form: LOZENGE
Manufacturer: Sato Pharmaceutical Co., Ltd.
Category: otc | Type: HUMAN OTC DRUG LABEL
Date: 20231128

ACTIVE INGREDIENTS: DEXTROMETHORPHAN HYDROBROMIDE 10 mg/1 1
INACTIVE INGREDIENTS: CETYLPYRIDINIUM CHLORIDE; LICORICE; HYDROXYPROPYL CELLULOSE; SILICON DIOXIDE; MAGNESIUM STEARATE; SUCROSE; ASPARTAME

Stona Troche

Active ingredients (in each lozenge)
Dextromethorphan HBr 10mg

Purpose
Cough suppressant

INDICATIONS AND USAGE

Uses temporarily relieves cough due to minor throat and bronchial irritation associated with
■a cold ■inhaled irritants

WARNINGS

Enter section text here

Do not use
■this product for persistent or chronic cough such as occurs with smoking, asthema, or emphysem, or if cough is accompanied by excessive phlegm (mucus) unless directed by a doctor.

Ask a doctor or pharmacist before use if
■you are now taking a prescription monoamine oxidase inhibitor (MAOI) (certain drugs for depression, psychiatric or emotional conditions, or Parkinson’s disease), or for 2 weeks after stopping the MAOI drug. If you do not know if your prescription drug contains an MAOI, ask a doctor or pharmacist before taking this product. A persistent cough may be a sign of a serious condition. If cough persists for more than 1 week, tends to recur, or is accompanied by fever, rash, or persistent headache, consult a doctor.

PREGNANCY OR BREAST FEEDING

If pregnant or breast-feeding, ask a health professional before use.

Keep out of reach of children. In case of accidental overdose, get medical help or contact a Poison Control Center right away.

Directions
Adults and children 12 years and older - Let 1 or 2 lozenges dissolve slowly in the mouth every 4 hours, not more than 12 lozenges in 24 hours.
Children 6 years to under 12 years - Let 1 lozenge dissolve slowly in the mouth every 4 hours, not more than 6 lozenges in 24 hours.
Children under 6 years - Ask a doctor
■once or twice daily, preferably morning and evening, when needed or as directed by a doctor
■start initial dosage with minimum dose, then adjust it to suit to bowel condition

Other information
■Phenylketonurics: Contains Phenylalanine (18.3mg) per lozenge.

INACTIVE INGREDIENT

Inactive ingredients aspartame, cetylpyridinium chloride, flavor, glycyrrhiza, hydroxypropyl cellulose, silicon dioxide, magnesium stearate, sucrose.

PACKAGE LABEL

stonatrochecart.jpg